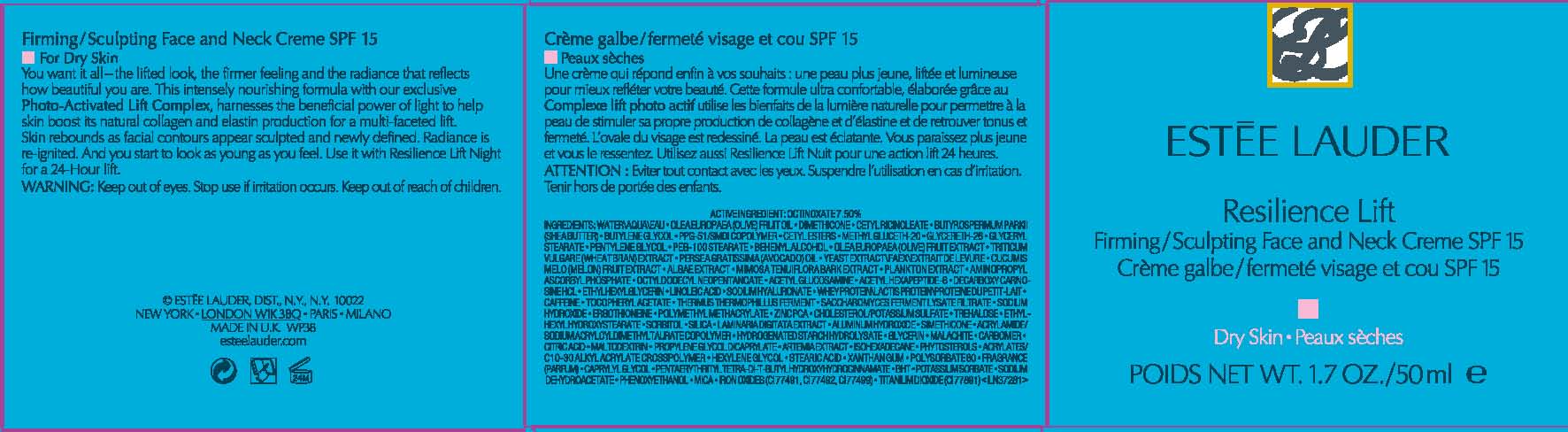 DRUG LABEL: RESILIENCE LIFT
NDC: 11559-012 | Form: CREAM
Manufacturer: ESTEE LAUDER INC
Category: otc | Type: HUMAN OTC DRUG LABEL
Date: 20110701

ACTIVE INGREDIENTS: OCTINOXATE 7.5 mL/100 mL
INACTIVE INGREDIENTS: WATER; CETYL ETHYLHEXANOATE; BUTYLENE GLYCOL; GLYCERYL MONOSTEARATE; PEG-100 STEARATE; OCTYLDODECYL NEOPENTANOATE; GLYCERIN; HYDROGENATED SOYBEAN LECITHIN; PENTYLENE GLYCOL; DOCOSANOL; SODIUM ALGINATE; AVOCADO OIL; MUSKMELON; POTASSIUM HYDROXIDE; MIMOSA TENUIFLORA BARK; YEAST; SACCHAROMYCES CEREVISIAE; CHOLESTEROL; POTASSIUM SULFATE; N-ACETYLGLUCOSAMINE; LINOLEIC ACID; LECITHIN, SOYBEAN; WHEY; ALPHA-TOCOPHEROL ACETATE; CAFFEINE; ERGOTHIONEINE; HYALURONATE SODIUM; STEARIC ACID; ZINC PIDOLATE; TREHALOSE; SORBITOL; ACETYL HEXAPEPTIDE-3; CITRIC ACID MONOHYDRATE; PROPYLENE GLYCOL DICAPRYLATE; MEDIUM-CHAIN TRIGLYCERIDES; MALTODEXTRIN; HEXYLENE GLYCOL; ETHYLHEXYLGLYCERIN; CAPRYLYL GLYCOL; CARBOMER HOMOPOLYMER TYPE C; SILICON DIOXIDE; ALUMINUM OXIDE; XANTHAN GUM; EDETATE DISODIUM; BUTYLATED HYDROXYTOLUENE; PHENOXYETHANOL; POTASSIUM SORBATE; SODIUM DEHYDROACETATE; MICA; FERRIC OXIDE RED; OLIVE OIL; DIMETHICONE; SHEA BUTTER; CETYL ESTERS WAX; METHYL GLUCETH-20

ACTIVE INGREDIENTS: OCTINOXATE 7.50%

INACTIVE INGREDIENT

INACTIVE INGREDIENTS: WATER\AQUA\EAU [] OLEA EUROPAEA (OLIVE) FRUIT OIL [] DIMETHICONE [] CETYL RICINOLEATE [] BUTYROSPERMUM PARKII (SHEA BUTTER) [] BUTYLENE GLYCOL [] PPG-51/SMDI COPOLYMER [] CETYL ESTERS [] METHYL GLUCETH-20 [] GLYCERETH-26 [] GLYCERYL STEARATE [] PENTYLENE GLYCOL [] PEG-100 STEARATE [] BEHENYL ALCOHOL [] OLEA EUROPAEA (OLIVE) FRUIT EXTRACT [] TRITICUM VULGARE (WHEAT BRAN) EXTRACT [] PERSEA GRATISSIMA (AVOCADO) OIL [] YEAST EXTRACT\FAEX\EXTRAIT DE LEVURE [] CUCUMIS MELO (MELON) FRUIT EXTRACT [] ALGAE EXTRACT [] MIMOSA TENUIFLORA BARK EXTRACT [] PLANKTON EXTRACT [] AMINOPROPYL ASCORBYL PHOSPHATE [] OCTYLDODECYL NEOPENTANOATE [] ACETYL GLUCOSAMINE [] ACETYL HEXAPEPTIDE-8 [] DECARBOXY CARNOSINE HCL [] ETHYLHEXYLGLYCERIN [] LINOLEIC ACID [] SODIUM HYALURONATE [] WHEY PROTEIN\LACTIS PROTEIN\PROTEINE DU PETIT-LAIT [] CAFFEINE [] TOCOPHERYL ACETATE [] THERMUS THERMOPHILLUS FERMENT [] SACCHAROMYCES FERMENT LYSATE FILTRATE [] SODIUM HYDROXIDE [] ERGOTHIONEINE [] POLYMETHYL METHACRYLATE [] ZINC PCA [] CHOLESTEROL/POTASSIUM SULFATE [] TREHALOSE [] ETHYLHEXYL HYDROXYSTEARATE [] SORBITOL [] SILICA [] LAMINARIA DIGITATA EXTRACT [] ALUMINA [] SIMETHICONE [] ACRYLAMIDE/SODIUM ACRYLOYLDIMETHYLTAURATE COPOLYMER [] HYDROGENATED STARCH HYDROLYSATE [] GLYCERIN [] MALACHITE [] CARBOMER [] CITRIC ACID [] MALTODEXTRIN [] PROPYLENE GLYCOL DICAPRYLATE [] ARTEMIA EXTRACT [] ISOHEXADECANE [] PHYTOSTEROLS [] ACRYLATES/C10-30 ALKYL ACRYLATE CROSSPOLYMER [] HEXYLENE GLYCOL [] STEARIC ACID [] XANTHAN GUM [] POLYSORBATE 80 [] FRAGRANCE (PARFUM) [] CAPRYLYL GLYCOL [] PENTAERYTHRITYL TETRA-DI-T-BUTYL HYDROXYHYDROCINNAMATE [] BHT [] POTASSIUM SORBATE [] SODIUM DEHYDROACETATE [] PHENOXYETHANOL [] MICA [] IRON OXIDES (CI 77491, CI 77492, CI 77499) [] TITANIUM DIOXIDE (CI 77891)

WARNINGS

WARNING: KEEP OUT OF EYES. STOP USE IF IRRITATION OCCURS. KEEP OUT OF REACH OF CHILDREN.

PACKAGE LABEL

PRINCIPAL DISPLAY PANEL:

ESTEE LAUDER

RESILIENCE LIFT

FIRMING/SCULPTING FACE AND NECK

LOTION

SPF15

FOR

DRY SKIN

NET WT. 1.7 OZ /50 ML

ESTEE LAUDER, DISTR

NEW YORK, NY 10022